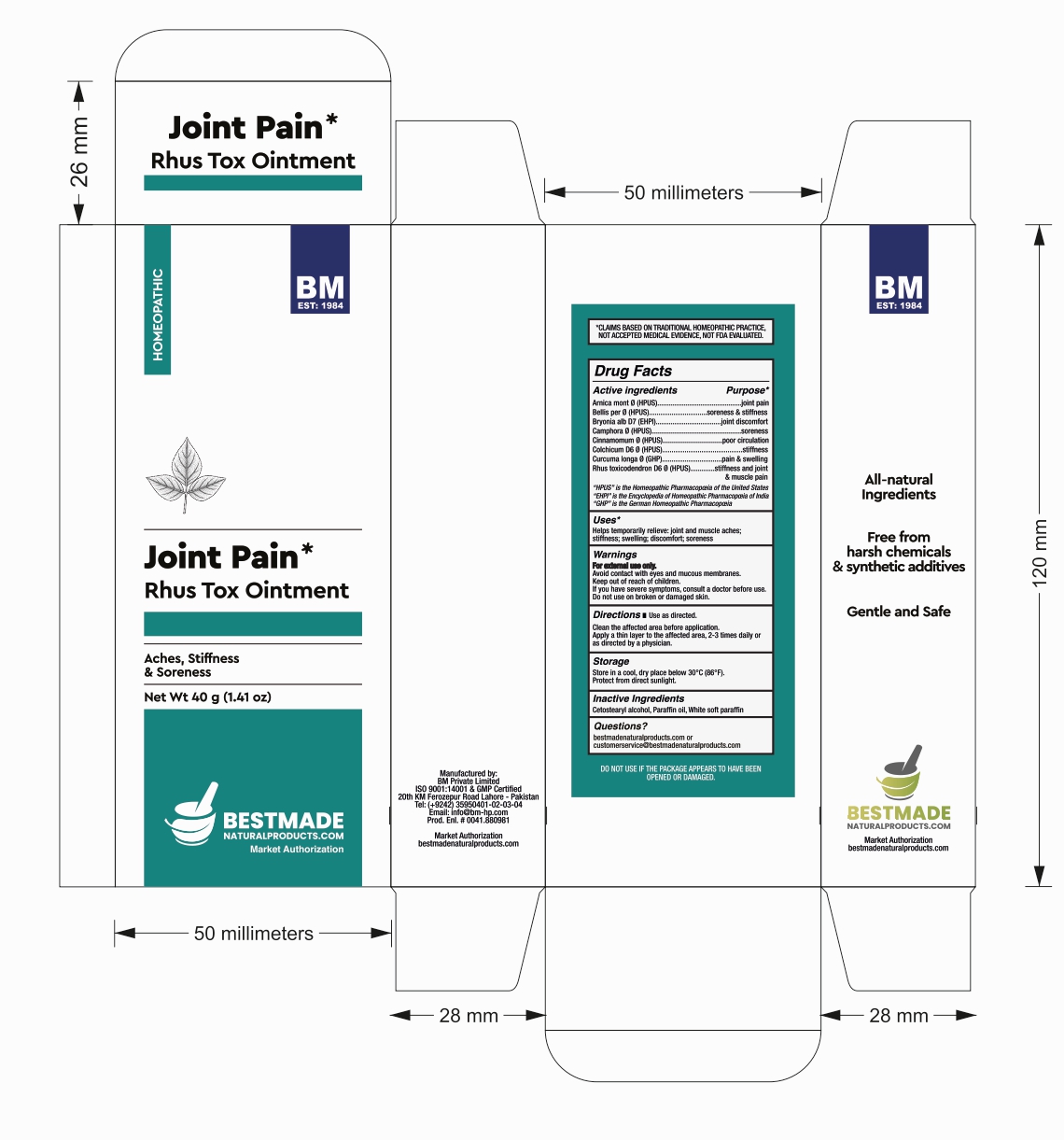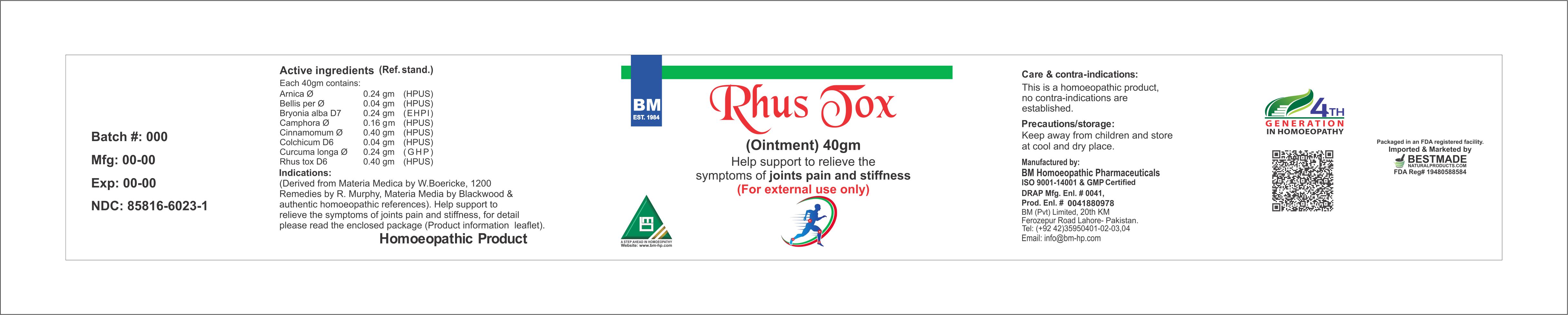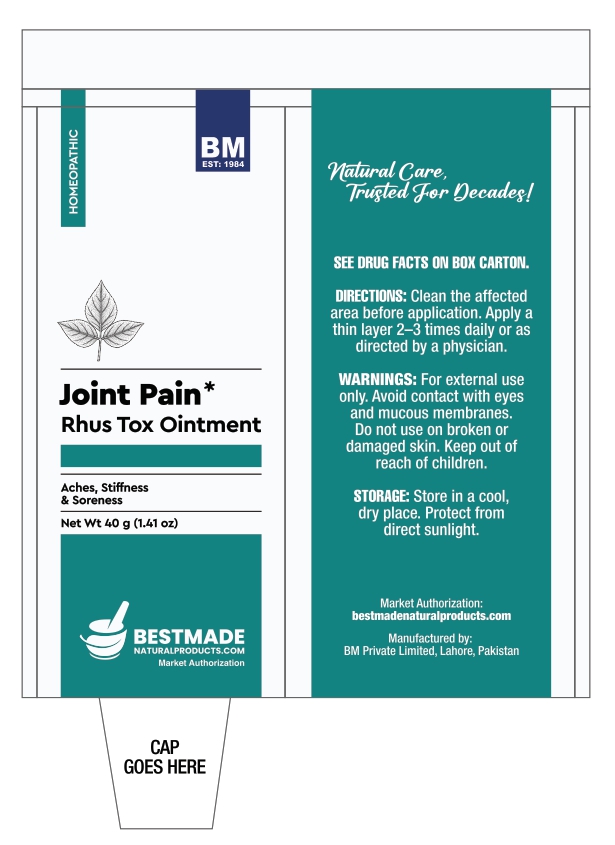 DRUG LABEL: BM Rhus Tox
NDC: 85816-6023 | Form: OINTMENT
Manufacturer: BM Private Limited
Category: homeopathic | Type: HUMAN OTC DRUG LABEL
Date: 20260212

ACTIVE INGREDIENTS: CINNAMON 1 [hp_X]/1 g; ARNICA MONTANA 1 [hp_X]/1 g; BELLIS PERENNIS 1 [hp_X]/1 g; BRYONIA ALBA ROOT 7 [hp_X]/1 g; CAMPHOR (NATURAL) 1 [hp_X]/1 g; TURMERIC 1 [hp_X]/1 g; COLCHICUM AUTUMNALE BULB 6 [hp_X]/1 g; TOXICODENDRON PUBESCENS LEAF 6 [hp_X]/1 g
INACTIVE INGREDIENTS: CETOSTEARYL ALCOHOL 0.095 g/1 g; MINERAL OIL 0.04 g/1 g; WHITE PETROLATUM 0.865 g/1 g

BM Rhus Tox Ointment

Inactive Ingredients:

Cetostearyl alcohol, Paraffin oil, White soft paraffin

Active ingredients

Arnica mont Ø (HPUS)

Bellis per Ø (HPUS)

Bryonia alb D7 (EHPI)

Camphora Ø (HPUS)

Cinnamomum Ø (HPUS)

Colchicum D6 (HPUS)

Curcuma longa Ø (GHP)

Rhus toxicodendron D6 Ø (HPUS)

Uses*

Helps temporarily relieve: joint and muscle aches; stiffness; swelling; discomfort; soreness

Active ingredients Purpose*

Arnica mont Ø (HPUS).................joint pain

Bellis per Ø (HPUS)....................soreness & stiffness

Bryonia alb D7 (EHPI)...............joint discomfort

Camphora Ø (HPUS).................soreness

Cinnamomum Ø (HPUS)...........poor circulation

Colchicum D6 (HPUS).............stiffness

Curcuma longa Ø (GHP)...........pain & swelling

Rhus toxicodendron D6 (HPUS).. stiffness and joint & muscle pain

Warnings:

Keep out of reach of children.

Warnings:

For external use only.

Avoid contact with eyes and mucous membranes.

Keep out of reach of children.

If you have severe symptoms, consult a doctor before use.

Do not use on broken or damaged skin.

Storage:

Store in a cool, dry place below 30°C (86°F).

Protect from direct sunlight.

Directions:

Use as directed.

Clean the affected area before application.

Apply a thin layer to the affected area, 2-3 times daily or as directed by a physician.

Package 1:

Package 2:

TUBE

BOX